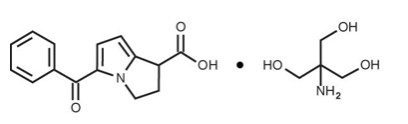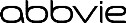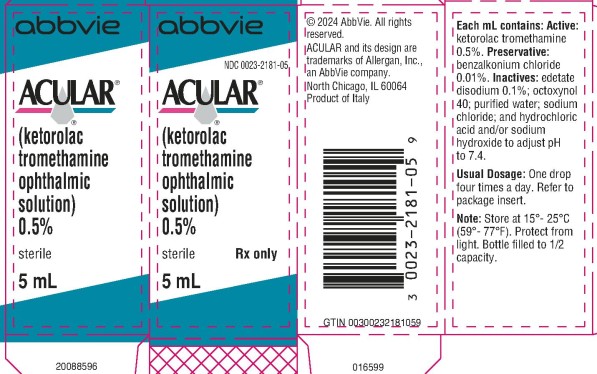 DRUG LABEL: Acular
NDC: 0023-2181 | Form: SOLUTION/ DROPS
Manufacturer: Allergan, Inc.
Category: prescription | Type: HUMAN PRESCRIPTION DRUG LABEL
Date: 20250918

ACTIVE INGREDIENTS: KETOROLAC TROMETHAMINE 5 mg/1 mL
INACTIVE INGREDIENTS: BENZALKONIUM CHLORIDE; EDETATE DISODIUM; OCTOXYNOL-40; WATER; SODIUM CHLORIDE; HYDROCHLORIC ACID; SODIUM HYDROXIDE

HIGHLIGHTS OF PRESCRIBING INFORMATION

These highlights do not include all the information needed to use ACULAR safely and effectively. See full prescribing information for ACULAR.
ACULAR® (ketorolac tromethamine ophthalmic solution) 0.5%, for topical ophthalmic use
Initial U.S. Approval: 1991

RECENT MAJOR CHANGES

Warnings and Precautions (5.5) 9/2025

1 INDICATIONS AND USAGE

ACULAR is a nonsteroidal anti-inflammatory drug (NSAID) indicated for:

- The temporary relief of ocular itching due to seasonal allergic conjunctivitis. (1)
- The treatment of inflammation following cataract surgery. (1)

2 DOSAGE AND ADMINISTRATION

- For temporary relief of ocular itching due to seasonal allergic conjunctivitis, apply one drop of ACULAR to the affected eye(s) four times a day.
- For the treatment of postoperative inflammation in patients who have undergone cataract extraction, apply one drop of ACULAR to the affected eye four times daily beginning 24 hours after cataract surgery and continuing through the first 2 weeks of the postoperative period. (2.1)

3 DOSAGE FORMS AND STRENGTHS

Ophthalmic solution containing 0.5% (5 mg/mL) ketorolac tromethamine. (3)

- 10 mL size bottle filled with 5 mL of solution

4 CONTRAINDICATIONS

Hypersensitivity to any component of this product. (4)

5 WARNINGS AND PRECAUTIONS

- Delayed healing (5.1)
- Cross-sensitivity or hypersensitivity (5.2)
- Increased bleeding time due to interference with thrombocyte aggregation (5.3)
- Corneal effects including keratitis (5.4)

6 ADVERSE REACTIONS

The most frequent adverse reactions reported by up to 40% of patients participating in clinical trials have been transient stinging and burning on instillation. (6.1)

To report SUSPECTED ADVERSE REACTIONS, contact AbbVie at 1-800-678-1605 or FDA at 1-800-FDA-1088 or www.fda.gov/medwatch.

FULL PRESCRIBING INFORMATION

1 INDICATIONS AND USAGE

ACULAR is indicated for the temporary relief of ocular itching due to seasonal allergic conjunctivitis. ACULAR is also indicated for the treatment of postoperative inflammation in patients who have undergone cataract extraction.

2 DOSAGE AND ADMINISTRATION

2.1 Recommended Dosage

Temporary Relief of Ocular Itching Due to Seasonal Allergic Conjunctivitis

The recommended dosage of ACULAR is one drop four times a day to the affected eye(s) for the temporary relief of ocular itching due to seasonal allergic conjunctivitis.

Treatment of Postoperative Inflammation in Patients Who Have Undergone Cataract Extraction

Apply one drop of ACULAR to the affected eye four times daily beginning 24 hours after cataract surgery and continuing through the first 2 weeks of the postoperative period for the treatment of postoperative inflammation in patients who have undergone cataract extraction.

2.2 Use with Other Topical Ophthalmic Medications

ACULAR has been safely administered in conjunction with other ophthalmic medications such as antibiotics, alpha-agonists, beta blockers, carbonic anhydrase inhibitors, cycloplegics, and mydriatics. Drops should be administered at least 5 minutes apart.

3 DOSAGE FORMS AND STRENGTHS

10 mL size bottle filled with 5 mL of ketorolac tromethamine ophthalmic solution, 0.5% (5 mg/mL).

4 CONTRAINDICATIONS

ACULAR solution is contraindicated in patients with previously demonstrated hypersensitivity to any of the ingredients in the formulation [see Adverse Reactions (6.1)].

5 WARNINGS AND PRECAUTIONS

5.1 Delayed Healing

Topical nonsteroidal anti-inflammatory drugs (NSAIDs) may slow or delay healing. Topical corticosteroids are also known to slow or delay healing. Concomitant use of topical NSAIDs and topical steroids may increase the potential for healing problems.

5.2 Cross-Sensitivity or Hypersensitivity

There is the potential for cross-sensitivity to acetylsalicylic acid, phenylacetic acid derivatives, and other NSAIDs. There have been reports of bronchospasm or exacerbation of asthma associated with the use of ketorolac tromethamine ophthalmic solution in patients who have either a known hypersensitivity to aspirin/non-steroidal anti-inflammatory drugs or a past medical history of asthma. Therefore, caution should be used when treating individuals who have previously exhibited sensitivities to these drugs.

5.3 Increased Bleeding Time

With some NSAIDs, there exists the potential for increased bleeding time due to interference with thrombocyte aggregation. There have been reports that ocularly applied nonsteroidal anti-inflammatory drugs may cause increased bleeding of ocular tissues (including hyphemas) in conjunction with ocular surgery.

It is recommended that ACULAR be used with caution in patients with known bleeding tendencies or who are receiving other medications, which may prolong bleeding time.

5.4 Corneal Effects

Use of topical NSAIDs may result in keratitis. In some susceptible patients, continued use of topical NSAIDs may result in epithelial breakdown, corneal thinning, corneal erosion, corneal ulceration, or corneal perforation. These events may be sight threatening. Patients with evidence of corneal epithelial breakdown should immediately discontinue use of topical NSAIDs and should be closely monitored for corneal health.

Postmarketing experience with topical NSAIDs suggests that patients with complicated ocular surgeries, corneal denervation, corneal epithelial defects, diabetes mellitus, ocular surface diseases (e.g., dry eye syndrome), rheumatoid arthritis, or repeat ocular surgeries within a short period of time may be at increased risk for corneal adverse events which may become sight threatening. Topical NSAIDs should be used with caution in these patients.

Postmarketing experience with topical NSAIDs also suggests that use more than 1 day prior to surgery or use beyond 14 days post-surgery may increase patient risk for the occurrence and severity of corneal adverse events.

5.5 Risk of Contamination

Avoid allowing the tip of the bottle to contact the eye or surrounding structures because this could cause the tip to become contaminated by common bacteria known to cause ocular infections. Serious damage to the eye and subsequent loss of vision may result from using contaminated solutions.

5.6 Contact Lens Wear

ACULAR should not be administered while wearing contact lenses.

6 ADVERSE REACTIONS

The following serious adverse reactions are described elsewhere in the labeling:

- Delayed Healing [see Warnings and Precautions (5.1)]
- Cross-Sensitivity or Hypersensitivity [see Warnings and Precautions (5.2)]
- Increased Bleeding Time [see Warnings and Precautions (5.3)]
- Corneal Effects [see Warnings and Precautions (5.4)]

6.1 Clinical Trials Experience

Because clinical trials are conducted under widely varying conditions, adverse reaction rates observed in the clinical trials of a drug cannot be directly compared to the rates in the clinical trials of another drug and may not reflect the rates observed in practice.

The most frequent adverse reactions reported with the use of ketorolac tromethamine ophthalmic solutions have been transient stinging and burning on instillation. These reactions were reported by up to 40% of patients participating in clinical trials.

Other adverse reactions occurring approximately 1% to 10% of the time during treatment with ketorolac tromethamine ophthalmic solutions included allergic reactions (including eye swelling, hyperemia, and pruritus), corneal edema, iritis, ocular inflammation, ocular irritation, ocular pain, superficial keratitis, and superficial ocular infections.

Other adverse reactions reported rarely with the use of ketorolac tromethamine ophthalmic solutions included: corneal infiltrates, corneal ulcer, eye dryness, headaches, and visual disturbance (blurry vision).

6.2 Postmarketing Experience

The following adverse reactions have been identified during postapproval use of ketorolac tromethamine ophthalmic solution 0.5% in clinical practice. Because these reactions are reported voluntarily from a population of uncertain size, it is not always possible to reliably estimate their frequency or establish a causal relationship to the drug.

Eye Disorders: corneal erosion, corneal perforation, corneal thinning, and epithelial breakdown.

Respiratory, Thoracic and Mediastinal Disorders: bronchospasm or exacerbation of asthma.

8 USE IN SPECIFIC POPULATIONS

8.1 Pregnancy

Risk Summary

There are no adequate and well-controlled studies with ACULAR in pregnant women. No evidence of teratogenicity has been observed in rats or rabbits with ACULAR at clinically relevant doses.

In the U.S. general population, the estimated background risk of major birth defects and miscarriage in clinically recognized pregnancies is 2% to 4% and 15% to 20%, respectively.

Clinical Considerations

Because of the known effects of prostaglandin-inhibiting drugs on the fetal cardiovascular system (closure of the ductus arteriosus), the use of ACULAR during late pregnancy should be avoided.

8.2 Lactation

Risk Summary

It is not known whether ketorolac when given topically is present in human milk. Because many drugs are excreted in human milk, caution should be exercised when ACULAR is administered to a nursing woman.

8.4 Pediatric Use

The safety and effectiveness of ACULAR have not been established in pediatric patients younger than 2 years old.

8.5 Geriatric Use

No overall differences in safety or effectiveness have been observed between elderly and other adult patients.

11 DESCRIPTION

ACULAR (ketorolac tromethamine ophthalmic solution) 0.5% is a member of the pyrrolo-pyrrole group of nonsteroidal anti-inflammatory drugs (NSAIDs) for topical ophthalmic use. Its chemical name is (±)-5-Benzoyl-2,3-dihydro-1H-pyrrolizine-1-carboxylic acid, compound with 2-amino-2-(hydroxymethyl)-1,3-propanediol (1:1) and it has the following structure:

ACULAR ophthalmic solution is supplied as a sterile isotonic aqueous 0.5% solution, with a pH of 7.4. ACULAR ophthalmic solution contains a racemic mixture of R-(+) and S-(-)- ketorolac tromethamine. Ketorolac tromethamine may exist in three crystal forms. All forms are equally soluble in water. The pKa of ketorolac is 3.5. This white to off-white crystalline substance discolors on prolonged exposure to light. The molecular weight of ketorolac tromethamine is 376.41. The osmolality of ACULAR ophthalmic solution is 290 mOsmol/kg.

Each mL of ACULAR ophthalmic solution contains: Active: ketorolac tromethamine 0.5%. Preservative: benzalkonium chloride 0.01%. Inactives: edetate disodium 0.1%; octoxynol 40; purified water; sodium chloride; hydrochloric acid and/or sodium hydroxide to adjust pH.

12 CLINICAL PHARMACOLOGY

12.1 Mechanism of Action

Ketorolac tromethamine is a nonsteroidal anti-inflammatory drug which, when administered systemically, has demonstrated analgesic, anti-inflammatory, and anti-pyretic activity. The mechanism of its action is thought to be due to its ability to inhibit prostaglandin biosynthesis.

12.3 Pharmacokinetics

Two drops of 0.5% ketorolac tromethamine ophthalmic solution instilled into the eyes of patients 12 hours and 1 hour prior to cataract extraction achieved a mean ketorolac concentration of 95 ng/mL in the aqueous humor of 8 of 9 eyes tested (range 40 to 170 ng/mL).

One drop of 0.5% ketorolac tromethamine ophthalmic solution was instilled into 1 eye and 1 drop of vehicle into the other eye TID in 26 healthy subjects. Five (5) of 26 subjects had detectable concentrations of ketorolac in their plasma (range 11 to 23 ng/mL) at Day 10 during topical ocular treatment. The range of concentrations following TID dosing of 0.5% ketorolac tromethamine ophthalmic solution are approximately 4 to 8% of the steady state mean minimum plasma concentration observed following four times daily oral administration of 10 mg ketorolac in humans (290 ± 70 ng/mL).

14 CLINICAL STUDIES

Two controlled clinical studies showed that ketorolac tromethamine ophthalmic solution was significantly more effective than its vehicle in relieving ocular itching caused by seasonal allergic conjunctivitis.

Two controlled clinical studies showed that patients treated for two weeks with ketorolac tromethamine ophthalmic solution were less likely to have measurable signs of inflammation (cell and flare) than patients treated with its vehicle.

Results from clinical studies indicate that ketorolac tromethamine has no significant effect upon intraocular pressure; however, changes in intraocular pressure may occur following cataract surgery.

16 HOW SUPPLIED/STORAGE AND HANDLING

ACULAR (ketorolac tromethamine ophthalmic solution) 0.5% is supplied sterile, in white opaque plastic (LDPE) bottles with white droppers, with gray high impact polystyrene (HIPS) caps as follows:

5 mL in 10 mL bottle NDC 0023-2181-05

Storage: Store at 15°C to 25°C (59°F to 77°F). Protect from light.

17 PATIENT COUNSELING INFORMATION

Slow or Delayed Healing

Advise patients of the possibility that slow or delayed healing may occur while using nonsteroidal anti-inflammatory drugs (NSAIDs).

Avoiding Contamination of the Product

Instruct patients to avoid allowing the tip of the bottle to contact the eye or surrounding structures because this could cause the tip to become contaminated by common bacteria known to cause ocular infections. Serious damage to the eye and subsequent loss of vision may result from using contaminated solutions.

Contact Lens Wear

Advise patients that ACULAR should not be administered while wearing contact lenses.

Intercurrent Ocular Conditions

Advise patients that if they develop an intercurrent ocular condition (e.g., trauma or infection) or have ocular surgery, they should immediately seek their physician’s advice concerning the continued use of ACULAR.

Concomitant Topical Ocular Therapy

Advise patients that if more than one topical ophthalmic medication is being used, the medicines should be administered at least 5 minutes apart.

Distributed by:
AbbVie Inc.
North Chicago, IL 60064

© 2025 AbbVie. All rights reserved.
ACULAR and its design are trademarks of Allergan, Inc., an AbbVie company.

20091161

PACKAGE LABEL

Principal Display Panel

NDC 0023-2181-05
abbvie
ACULAR®
(ketorolac
tromethamine
ophthalmic
solution)
0.5%
sterile Rx only
5 mL